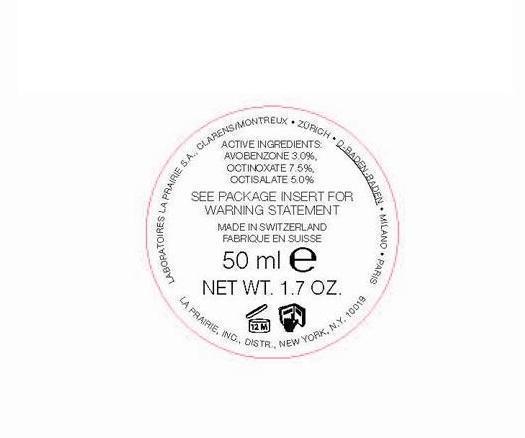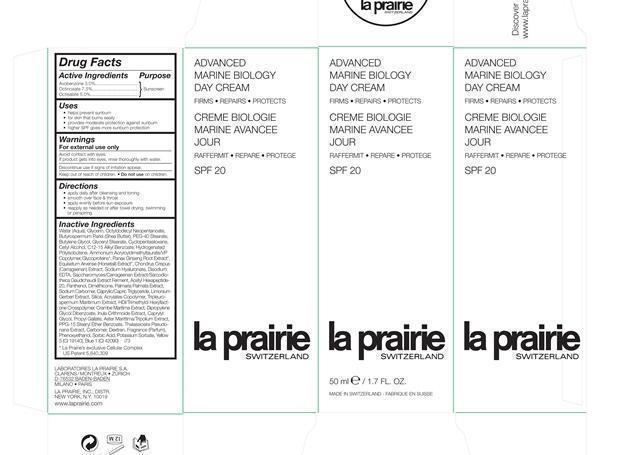 DRUG LABEL: Advanced Marine Biology Day SPF 20
NDC: 68807-319 | Form: CREAM
Manufacturer: Temmentec Ag
Category: otc | Type: HUMAN OTC DRUG LABEL
Date: 20160125

ACTIVE INGREDIENTS: AVOBENZONE 3 g/100 kg; OCTINOXATE 7.5 g/100 kg; OCTISALATE 5 g/100 kg
INACTIVE INGREDIENTS: WATER; OCTYLDODECYL NEOPENTANOATE; SHEA BUTTER; PEG-40 STEARATE; BUTYLENE GLYCOL; GLYCERYL MONOSTEARATE; CYCLOMETHICONE 5; CETYL ALCOHOL; C12-15 ALKYL BENZOATE; HYDROGENATED POLYBUTENE (1300 MW); AMMONIUM ACRYLOYLDIMETHYLTAURATE/VP COPOLYMER; ASIAN GINSENG; CHONDRUS CRISPUS; HYALURONATE SODIUM; EDETATE DISODIUM; PANTHENOL; DIMETHICONE; DULSE; MEDIUM-CHAIN TRIGLYCERIDES; LIMONIUM GERBERI FLOWERING TOP; SILICON DIOXIDE; DIPROPYLENE GLYCOL DIBENZOATE; CAPRYLYL GLYCOL; PROPYL GALLATE; PPG-15 STEARYL ETHER BENZOATE; CARBOMER HOMOPOLYMER TYPE B (ALLYL SUCROSE CROSSLINKED); PHENOXYETHANOL; SORBIC ACID; POTASSIUM SORBATE; FD&C YELLOW NO. 5; FD&C BLUE NO. 1

Advanced Marine Biology Day Cream SPF 20

Active Ingredients Purpose

Avobenzone 3.0% Sunscreen

Octinoxate 7.5% Sunscreen

Octisalate 5.0% Sunscreen

Uses

- helps prevent sunburn
- for skin that burns easily
- provides moderate protection against sunburn
- higher SPF gives more sunburn protection

Keep out of reach of children. Do not use on children.

INDICATIONS AND USAGE

Discontinue use if signs of irritation occur

Warnings

For External use only

Avoid Contact with eyes

If product gets into eyes, rinse thoroughly with water

Directions

- apply daily after cleansing and toning
- smooth over face and throat
- apply evenly before sun exposure
- reapply as needed or after towel drying, swimming or perspiring

Inactive Ingredients

Water (Aqua), Glycerin, Octyldodecyl Neopentanoate, Butyrospermum Parkii (Shea Butter), PEG-40 Stearate, Butylene Glycol, Glyceryl Stearate, Cyclopentasiloxane, Cetyl Alcohol, C12-15 Alkyl Benzoate, Hydrogenated Polyisobutene, Ammonium Acryloyldimethyltaurate/VP Copolymer, Glycoproteins*, Panax Ginseng Root Extract, Equisetum Arvense (Horsetail) Extract, Chondrus Crispus (Carrageenan) Extract, Sodium Hyaluronate, Disodium EDTA, Saccharomyces/Carrageenan Extract/Sarcodiotheca Gaudichaudii Extract Ferment, Acetyl Hexapeptide-20, Panthenol, Dimethicone, Palmaria Palmata Extract, Sodium Carbomer, Caprylic/Capric Triglyceride, Limonium Gerberi Extract, Silica, Acrylates Copolymer, Tripleurospermum Maritimum Extract, HDI/Trimethylol Hexyllactone Crosspolymer, Crambe Maritima Extract, Dipropylene Glycol Dibenzoate, Inula Crithmoide Extract, Caprylyl Glycol, Propyl Gallate, Aster Marittima/Tripolium Extract, PPG-15 Stearyl Ether Benzoate, Thalassiosira Pseudonana Extract, Carbomer, Dextran, Fragrance (Parfum), Phenoxyethanol, Sorbic Acid, Potassium Sorbate, Yellow 5 (CI 19140), Blue 1 (CI 42090)

PACKAGE LABEL

Advanced Marine Biology Day Cream

Firms Repairs Protects

Creme Biologie Marine Acancee Jour

Raffermit Repare Protege

SPF 20

La Prairie Switzerland

50 ml / 1.7 Fl. Oz.